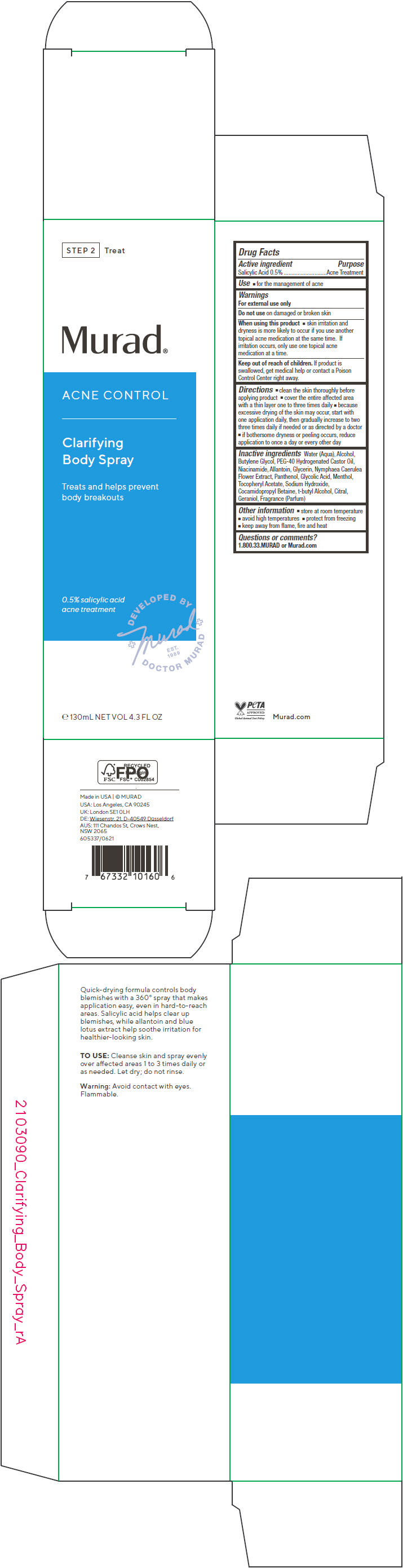 DRUG LABEL: Acne Control Clarifying Body Spry
NDC: 70381-112 | Form: SPRAY
Manufacturer: Murad, LLC
Category: otc | Type: HUMAN OTC DRUG LABEL
Date: 20210702

ACTIVE INGREDIENTS: SALICYLIC ACID 0.5 g/100 mL
INACTIVE INGREDIENTS: WATER; ALCOHOL; BUTYLENE GLYCOL; POLYOXYL 40 HYDROGENATED CASTOR OIL; NIACINAMIDE; ALLANTOIN; GLYCERIN; NYMPHAEA CAERULEA FLOWER; PANTHENOL; GLYCOLIC ACID; MENTHOL, UNSPECIFIED FORM; .ALPHA.-TOCOPHEROL ACETATE; SODIUM HYDROXIDE; COCAMIDOPROPYL BETAINE; TERT-BUTYL ALCOHOL; CITRAL; GERANIOL

Acne Control Clarifying Body Spray

Drug Facts

Active ingredient

Salicylic Acid 0.5%

Purpose

Acne Treatment

Use

- for the management of acne

Warnings

For external use only

Do not use on damaged or broken skin

When using this product

- skin irritation and dryness is more likely to occur if you use another topical acne medication at the same time. If irritation occurs, only use one topical acne medication at a time.

Keep out of reach of children. If product is swallowed, get medical help or contact a Poison Control Center right away.

Directions

- clean the skin thoroughly before applying product
- cover the entire affected area with a thin layer one to three times daily
- because excessive drying of the skin may occur, start with one application daily, then gradually increase to two three times daily if needed or as directed by a doctor
- if bothersome dryness or peeling occurs, reduce application to once a day or every other day

Inactive ingredients

Water (Aqua), Alcohol, Butylene Glycol, PEG-40 Hydrogenated Castor Oil, Niacinamide, Allantoin, Glycerin, Nymphaea Caerulea Flower Extract, Panthenol, Glycolic Acid, Menthol, Tocopheryl Acetate, Sodium Hydroxide, Cocamidopropyl Betaine, t-butyl Alcohol, Citral, Geraniol, Fragrance (Parfum)

Other information

- store at room temperature
- avoid high temperatures
- protect from freezing
- keep away from ﬂame, ﬁre and heat

Questions or comments?

1.800.33.MURAD or Murad.com

PRINCIPAL DISPLAY PANEL - 130 mL Bottle Carton

STEP 2
Treat

Murad®

ACNE CONTROL

Clarifying
Body Spray

Treats and helps prevent
body breakouts

0.5% salicylic acid
acne treatment

DEVELOPED BY
+Murad+
EST.
1989
DOCTOR MURAD

e 130mL NET VOL 4.3 FL OZ